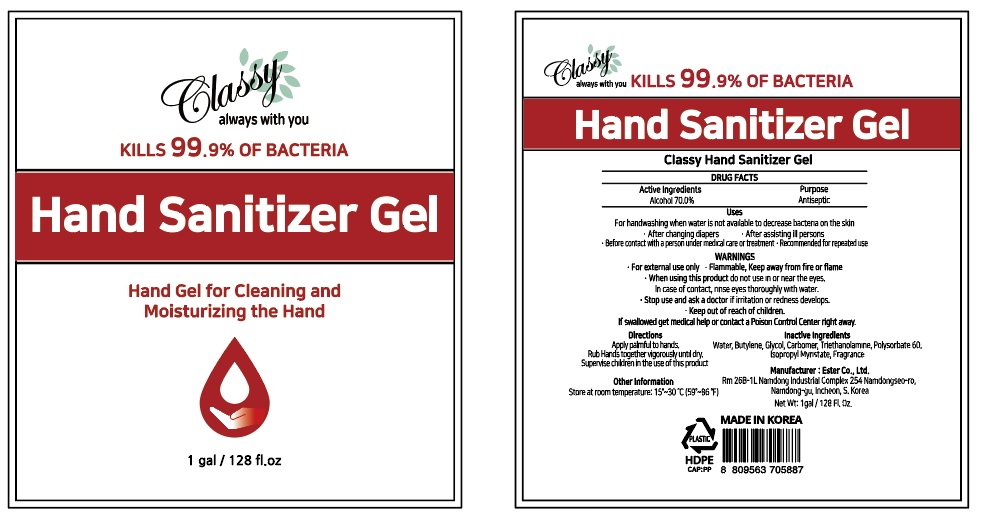 DRUG LABEL: Classy Hand Sanitizer Gel
NDC: 74004-128 | Form: GEL
Manufacturer: Ester Co., Ltd.
Category: otc | Type: HUMAN OTC DRUG LABEL
Date: 20200604

ACTIVE INGREDIENTS: ALCOHOL 2649.5 mL/3785 mL
INACTIVE INGREDIENTS: POLYSORBATE 60; BUTYLENE GLYCOL; ISOPROPYL MYRISTATE; CARBOMER HOMOPOLYMER, UNSPECIFIED TYPE; WATER; TROLAMINE

[Ester Co., Ltd.-Classy Hand Sanitizer Gel] 1 Gallon : 74004-128-01